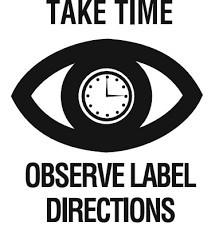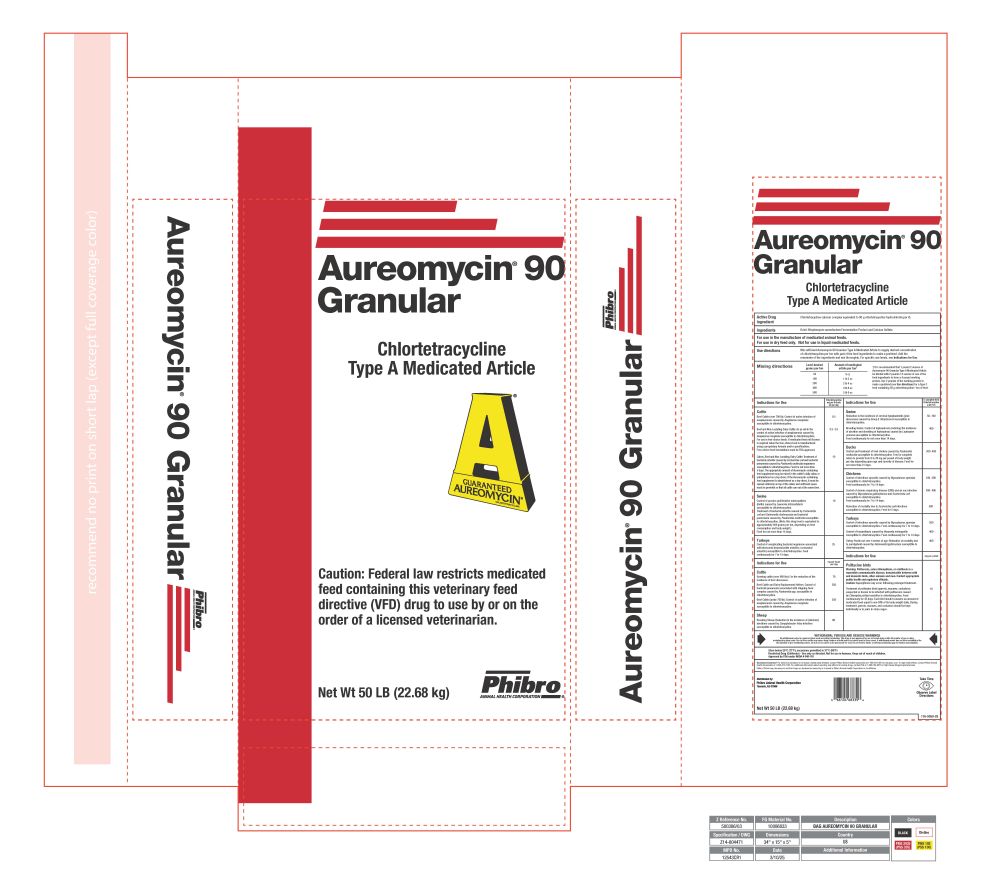 DRUG LABEL: Aureomycin
NDC: 66104-1005 | Form: GRANULE
Manufacturer: Phibro Animal Health
Category: animal | Type: VFD TYPE A MEDICATED ARTICLE ANIMAL DRUG LABEL
Date: 20260224

ACTIVE INGREDIENTS: CHLORTETRACYCLINE HYDROCHLORIDE 90 g/0.45 kg

Aureomycin® 90 Granular

Aureomycin® 90 Granular

Chlortetracycline
Type A Medicated Article

Caution: Federal law restricts medicated feed containing this veterinary feed directive (VFD) drug to use by or on the order of a licensed veterinarian.

Net Wt 50 LB (22.68 kg)

Active drug ingredient

Chlortetracycline calcium complex equivalent to 90 g chlortetracycline hydrochloride per lb.

Ingredients

Dried Streptomyces aureofaciens Fermentation Product and Calcium Sulfate.

PURPOSE

For use in the manufacture of medicated animal feeds.
For use in dry feed only. Not for use in liquid medicated feeds.

Use directions

Mix sufficient Aureomycin 90 Granular Type A Medicated Article to supply desired concentration of chlortetracycline per ton with part of the feed ingredients to make a preblend. Add the remainder of the ingredients and mix thoroughly. For specific use levels, see Indications for use.

Mixing directions

Level desired grams per ton | Amount of medicated article per ton †
50 | 9 oz
100 | 1 lb 2 oz
200 | 2 lb 4 oz
400 | 4 lb 8 oz
500 | 5 lb 9 oz

† It is recommended that 1 pound 2 ounces of Aureomycin 90 Granular Type A Medicated Article be diluted with 2 pounds 14 ounces of one of the feed ingredients to form a 4 pound working premix. Use 2 pounds of the working premix to make a preblend (see Use directions) for a Type C feed containing 50 g chlortetracycline / ton of feed

Indications for use | Chlortetracycline mg per lb body wt per day
Cattle
Beef Cattle (over 700 lb): Control of active infection of anaplasmosis caused by Anaplasma marginale susceptible to chlortetracycline. | 0.5
Beef and Non-Lactating Dairy Cattle: As an aid in the control of active infection of anaplasmosis caused by Anaplasma marginale susceptible to chlortetracycline. For use in free-choice feeds. A medicated feed mill license is required when the free-choice feed is manufactured using a proprietary formula and/or specifications. Free-choice feed formulations must be FDA-approved. | 0.5-2.0
Calves, Beef and Non-Lactating Dairy Cattle: Treatment of bacterial enteritis caused by Escherichia coli and bacterial pneumonia caused by Pasteurella multocida organisms susceptible to chlortetracycline. Feed for not more than 5 days. The appropriate amount of Aureomycin-containing feed supplement may be mixed in the cattle's daily ration or administered as a top-dress. If the Aureomycin-containing feed supplement is administered as a top-dress, it must be spread uniformly on top of the ration and sufficient space must be provided so that all cattle can eat at the same time. | 10
Swine
Control of porcine proliferative enteropathies (ileitis) caused by Lawsonia intracellularis susceptible to chlortetracycline. Treatment of bacterial enteritis caused by Escherichia coli and Salmonella choleraesuis and bacterial pneumonia caused by Pasteurella multocida susceptible to chlortetracycline. (Note: this drug level is equivalent to approximately 400 grams per ton, depending on feed consumption and body weight.) Feed for not more than 14 days. | 10
Turkeys
Control of complicating bacterial organisms associated with bluecomb (transmissible enteritis; coronaviral enteritis) susceptible to chlortetracycline. Feed continuously for 7 to 14 days. | 25
Indications for use | mg per head per day
Cattle
Growing Cattle (over 400 lb): For the reduction of the incidence of liver abscesses. | 70
Beef Cattle and Dairy Replacement Heifers: Control of bacterial pneumonia associated with shipping fever complex caused by Pasteurella spp. susceptible to chlortetracycline. | 350
Beef Cattle (under 700 lb): Control of active infection of anaplasmosis caused by Anaplasma marginale susceptible to chlortetracycline. | 350
Sheep
Breeding Sheep: Reduction in the incidence of (vibrionic) abortions caused by Campylobacter fetus infection susceptible to chlortetracycline. | 80
Indications for use | In complete feed Chlortetracycline g per ton
Swine
Reduction in the incidence of cervical lymphadenitis (jowl abscesses) caused by Group E Streptococci susceptible to chlortetracycline. | 50-100
Breeding Swine: Control of leptospirosis (reducing the incidence of abortion and shedding of leptospirae) caused by Leptospira pomona susceptible to chlortetracycline. Feed continuously for not more than 14 days. | 400
Ducks
Control and treatment of fowl cholera caused by Pasteurella multocida susceptible to chlortetracycline. Feed in complete ration to provide from 8 to 28 mg per pound of body weight per day depending upon age and severity of disease. Feed for not more than 21 days. | 200-400
Chickens
Control of infectious synovitis caused by Mycoplasma synoviae susceptible to chlortetracycline. Feed continuously for 7 to 14 days. | 100-200
Control of chronic respiratory disease (CRD) and air sac infection caused by Mycoplasma gallisepticum and Escherichia coli susceptible to chlortetracycline. Feed continuously for 7 to 14 days. | 200-400
Reduction of mortality due to Escherichia coli infections susceptible to chlortetracycline. Feed for 5 days. | 500
Turkeys
Control of infectious synovitis caused by Mycoplasma synoviae susceptible to chlortetracycline. Feed continuously for 7 to 14 days. | 200
Control of hexamitiasis caused by Hexamita meleagridis susceptible to chlortetracycline. Feed continuously for 7 to 14 days. | 400
Turkey Poults not over 4 weeks of age: Reduction of mortality due to paratyphoid caused by Salmonella typhimurium susceptible to chlortetracycline. | 400
Indications for use | mg per g feed
Psittacine birds
Warning: Psittacosis, avian chlamydiosis, or ornithosis is a reportable communicable disease, transmissible between wild and domestic birds, other animals and man. Contact appropriate public health and regulatory officials.
Caution: Aspergilliosis may occur following prolonged treatment.
Treatment of psittacine birds (parrots, macaws, cockatoos) suspected or known to be infected with psittacosis caused by Chlamydia psittaci sensitive to chlortetracycline. Feed continuously for 45 days. Each bird should consume an amount of medicated feed equal to one-fifth of its body weight daily. During treatment, parrots, macaws, and cockatoos should be kept individually or in pairs in clean cages. | 10

Withdrawal Periods and Residue Warnings

No withdrawal period is required when used according to labeling. This drug is not approved for use in female dairy cattle 20 months of age or older, including dry dairy cows. Use in these cattle may cause drug residues in milk and/or in calves born to these cows. A withdrawal period has not been established for this product in pre-ruminating calves. Do not use in calves to be processed for veal. Do not feed to ducks or turkeys producing eggs for human consumption.

Storage

Store below 25°C (77°F), excursions permitted to 37°C (99°F)
Restricted Drug (California) - Use only as directed. Not for use in humans. Keep out of reach of children.
Approved by FDA under NADA # 048-761

Questions/Comments? For technical assistance or to obtain a Safety Data Sheet(s), contact Phibro Animal Health Corporation at 1-888-403-0074 or ww.pahc.com. To report side effects, contact Phibro Animal
Health Corporation at 1-888-475-7355. For additional information about reporting side effects for animal drugs, contact FDA at 1-888-FDA-VETS or http://www.fda.gov/reportanimalae

Phibro, Phibro logo, Aureomycin and the A logo are trademarks owned by or licensed to Phibro Animal Health Corporation or its affiliates.

Distributed by:

Phibro Animal Health Corporation

Teaneck, NJ 07666

176-9050-02

Take Time Statement

PRINCIPAL DISPLAY PANEL

Aureomycin 90 G Label